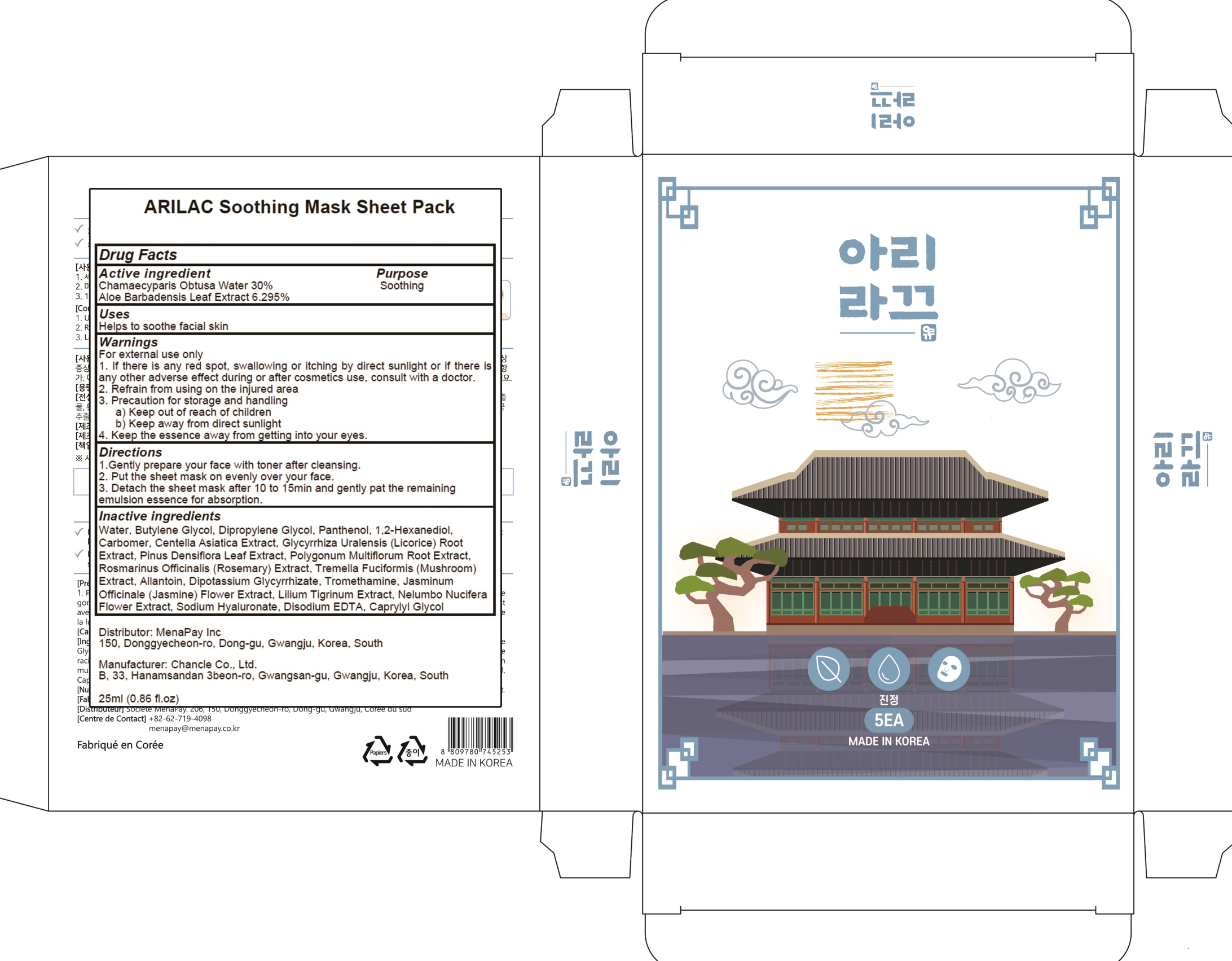 DRUG LABEL: ARILAC Soothing Mask Sheet Pack
NDC: 81758-030 | Form: PATCH
Manufacturer: Menapay Inc.
Category: otc | Type: HUMAN OTC DRUG LABEL
Date: 20210513

ACTIVE INGREDIENTS: CHAMAECYPARIS OBTUSA WOOD OIL 30.0 g/100 mL; ALOE VERA LEAF 6.295 g/100 mL
INACTIVE INGREDIENTS: Water; Butylene Glycol

ACTIVE INGREDIENT

Chamaecyparis Obtusa Water 30%
Aloe Barbadensis Leaf Extract 6.295%

INACTIVE INGREDIENTS

Water, Butylene Glycol, Dipropylene Glycol, Panthenol, 1,2-Hexanediol, Carbomer, Centella Asiatica Extract, Glycyrrhiza Uralensis (Licorice) Root Extract, Pinus Densiflora Leaf Extract, Polygonum Multiflorum Root Extract, Rosmarinus Officinalis (Rosemary) Extract, Tremella Fuciformis (Mushroom) Extract, Allantoin, Dipotassium Glycyrrhizate, Tromethamine, Jasminum Officinale (Jasmine) Flower Extract, Lilium Tigrinum Extract, Nelumbo Nucifera Flower Extract, Sodium Hyaluronate, Disodium EDTA, Caprylyl Glycol

PURPOSE

Soothing

WARNINGS

For external use only
1. If there is any red spot, swallowing or itching by direct sunlight or if there is any other adverse effect during or after cosmetics use, consult with a doctor.
2. Refrain from using on the injured area
3. Precaution for storage and handling
a) Keep out of reach of children
b) Keep away from direct sunlight
4. Keep the essence away from getting into your eyes.

KEEP OUT OF REACH OF CHILDREN

Uses

Helps to soothe facial skin

Directions

1. Gently prepare your face with toner after cleansing.
2. Put the sheet mask on evenly over your face.
3. Detach the sheet mask after 10 to 15min and gently pat the remaining emulsion essence for absorption.